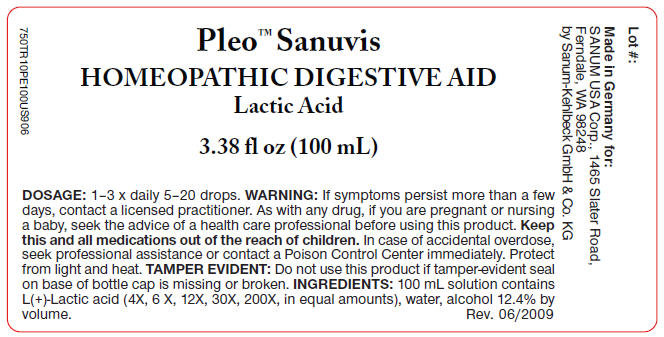 DRUG LABEL: Pleo Sanuvis
NDC: 60681-6300 | Form: KIT | Route: ORAL
Manufacturer: Sanum Kehlbeck GmbH & Co. KG
Category: homeopathic | Type: HUMAN OTC DRUG LABEL
Date: 20091007

ACTIVE INGREDIENTS: lactic acid, l- 4 [hp_X]/100 mL; lactic acid, l- 6 [hp_X]/100 mL; lactic acid, l- 12 [hp_X]/100 mL; lactic acid, l- 30 [hp_X]/100 mL; lactic acid, l- 200 [hp_X]/100 mL
INACTIVE INGREDIENTS: water; alcohol; water; alcohol; water; alcohol; water; alcohol; water; alcohol

Pleo™ Sanuvis

Homeopathic Digestive Aid Lactic Acid

3.38 fl oz
(100 mL)

INGREDIENTS

100mL solution contains L-Lactic acid (4X, 6X, 12X, 30X, 200X, in equal amounts), in a base of purified water, alcohol 12.4% by volume.

Tamper evident

Do not use this product if tamper-evident seal on base of bottle cap is missing or broken or if imprinted security strip on carton is torn.

DOSAGE

1-3 × daily 5-20 drops.

WARNING

If symptoms persist more than a few days, contact a licensed practitioner. As with any other drug, if you are pregnant or nursing a baby, seek the advice of a health care professional before using this product.

KEEP OUT OF REACH OF CHILDREN

Keep this and all medications out of the reach of children. In case of accidental overdose, seek professional assistance or contact a Poison Control Center immediately.

STORAGE AND HANDLING

Protect from light and heat.

Made in Germany

Distributed by:
SANUM USA Corp.
1465 Slater Road
Ferndale, WA 98248

Manufactured By:
Sanum-Kehlbeck
GmbH & Co. KG

Rev. 12/2007

PRINCIPAL DISPLAY PANEL - 100 mL Label

Pleo™ Sanuvis

HOMEOPATHIC DIGESTIVE AID
Lactic Acid

3.38 fl oz (100 mL)

DOSAGE: 1–3 x daily 5–20 drops. WARNING: If symptoms persist more than a few
days, contact a licensed practitioner. As with any drug, if you are pregnant or nursing
a baby, seek the advice of a health care professional before using this product. Keep
this and all medications out of the reach of children. In case of accidental overdose,
seek professional assistance or contact a Poison Control Center immediately. Protect
from light and heat. TAMPER EVIDENT: Do not use this product if tamper-evident seal
on base of bottle cap is missing or broken. INGREDIENTS: 100 mL solution contains
L(+)-Lactic acid (4X, 6 X, 12X, 30X, 200X, in equal amounts), water, alcohol 12.4% by
volume.
Rev. 06/2009